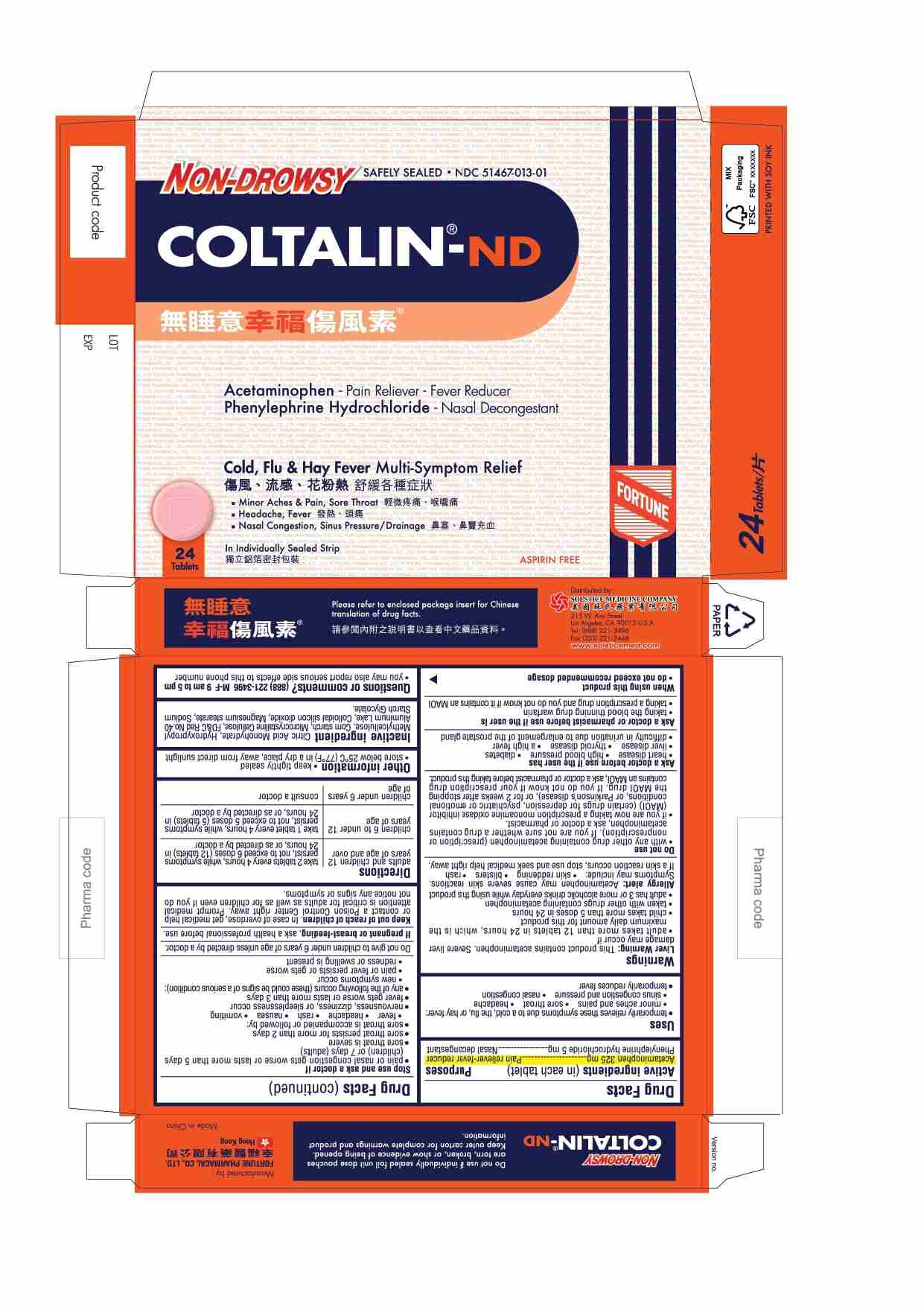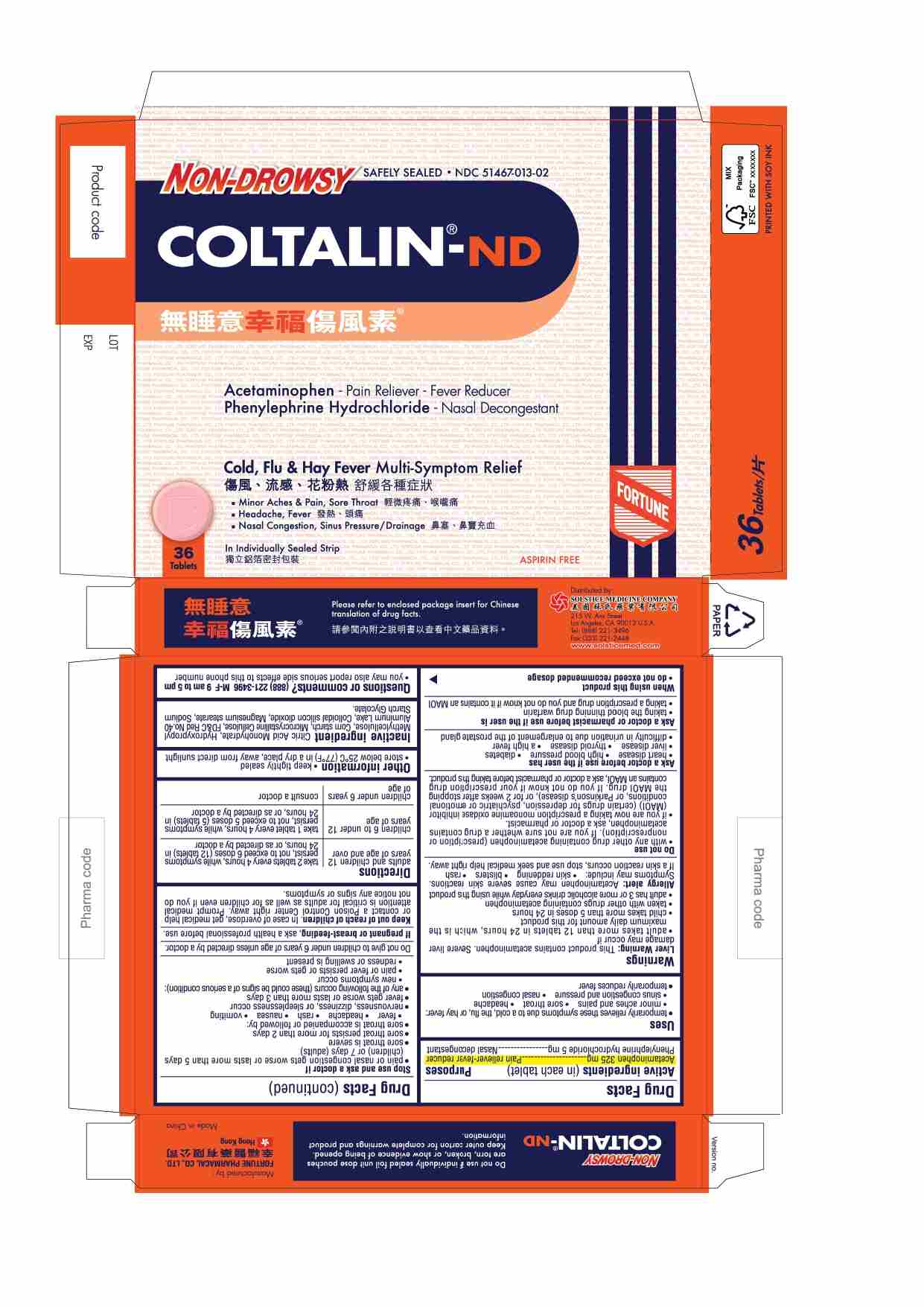 DRUG LABEL: COLTALIN-ND
NDC: 51467-013 | Form: TABLET
Manufacturer: FORTUNE PHARMACAL COMPANY LIMITED
Category: otc | Type: HUMAN OTC DRUG LABEL
Date: 20260213

ACTIVE INGREDIENTS: ACETAMINOPHEN 325 mg/1 1; PHENYLEPHRINE HYDROCHLORIDE 5 mg/1 1
INACTIVE INGREDIENTS: MICROCRYSTALLINE CELLULOSE; CITRIC ACID MONOHYDRATE; SILICON DIOXIDE; STARCH, CORN; FD&C RED NO. 40; MAGNESIUM STEARATE; SODIUM STARCH GLYCOLATE TYPE A POTATO; HYDROXYPROPYL METHYLCELLULOSE

Drug Facts

Active ingredients(in each tablet)
Acetaminophen 325 mg
Phenylephrine hydrochloride 5 mg

Purpose
Pain reliever-fever reducer
Nasal decongestant

Uses
■ temporarily relieves these symptoms due to a cold, the flu, or hay fever:
■ minor aches and pains
■ sore throat
■ headache
■ sinus congestion and pressure
■ nasal congestion
■ temporarily reduces fever

Warnings

Liver Warning: This product contains acetaminophen. Severe liver damage may occur if

- adult takes more than 12 tablets in 24 hours, which is the maximum daily amount for this product
- child takes more than 5 doses in 24 hours
- taken with other drugs containing acetaminophen
- adult has 3 or more alcoholic drinks everyday while using this product

Allergy alert: Acetaminophen may cause severe skin reactions.

Symptoms may include:

- skin reddening
- blisters
- rash

If a skin rash occurs, stop use and seek medical help right away.

Do not use
■ with any other drug containing acetaminophen (prescription or nonprescription). If you are not sure whether a drug contains acetaminophen, ask a doctor or pharmacist.
for fever for more than 3 days, unless directed by a physician
■ if you are now taking a prescription monoamine oxidase inhibitor (MAOI) (certain drugs for depression, psychiatric or emotional conditions, or Parkinson's disease), or for 2 weeks after stopping the MAOI drug. If you do not know whether a prescription drug contains an MAOI, ask a doctor or pharmacist before taking this product.

Ask a doctor before use if the user has
■ heart disease
■ high blood pressure
■ diabetes
■ glaucoma
■ liver disease
■ thyroid disease
■ a high fever
■ difficulty in urination due to enlargement of the prostate gland

Ask a doctor or pharmacist before use if the user is
■ taking the blood thinning drug warfarin
■ taking a prescription drug and you do not know if it contains an MAOI

When using this product
■ do not exceed recommended dosage

Stop use and ask a doctor if
■ pain or nasal congestion gets worse or lasts more than 5 days (children) or 7 days (adults)
■ sore throat is severe
■ sore throat persists for more than 2 days
■ sore throat is accompanied or followed by:
■ fever
■ headache
■ rash
■ nausea
■ vomiting
■ nervousness, dizziness, or sleeplessness occur
■ fever gets worse or lasts more than 3 days
■ any of the following occurs (these could be signs of a serious condition):
■ new symptoms occur
■ pain or fever persist or gets worse
■ redness or swelling is present

WARNINGS

Do not give to children under 6 years of age unless directed by a doctor.

PREGNANCY OR BREAST FEEDING

If pregnant or breast-feeding,ask a health professional before use.

Keep out of reach of children.In case of overdose, get medical help or contact a Poison Control Center right away.
Prompt medical attention is critical for adults as well as children even if you do not notice any signs or symptoms.

Directions
■ adults and children 12 years of age and over: 2 tablets every 4 hours, while symptoms persist, not to exceed 6 doses (12 tablets) in 24 hours, or as directed by a doctor
■ children 6 to under 12 years of age: 1 tablet every 4 hours, while symptoms persist, not to exceed 5 doses (5 tablets) in 24 hours, or as directed by a doctor
■ children under 6 of age : consult a doctor

Other information
■ keep tightly sealed
■ store between below 25 C (77 F) in a dry place, away from direct sunlight

Inactive ingredients
Citric Acid Monohydrate, Hydroxypropyl Methylcellulose, Corn starch, Microcrystalline Cellulose, FD&C red no. 40 aluminum lake, Colloidal silicon dioxide, Magnesium stearate, Sodium starch glycolate

Questions or comments? (888) 221-3496 M-F 9 am to 5 pm
■ you may also report serious side effects to this phone number

PACKAGE LABEL

COLTALIN-ND

Non-Drowsy

Safely Sealed

NDC 51467-013-01

Acetaminophen - Pain Reliever-Fever Reducer
Phenylephrine Hydrochloride - Nasal Decongestant

Cold, Flu & Hay Fever Multi-Symptom Relief
■ Minor Aches & Pain, Sore Throat
■ Headache, Fever
■ Nasal Congestion, Sinus Pressure/Drainage

24 Tablets

In Individually Sealed Strip

Aspirin Free

PACKAGE LABEL

COLTALIN-ND

Non-Drowsy

Safely Sealed

NDC 51467-013-02

Acetaminophen - Pain Reliever-Fever Reducer
Phenylephrine Hydrochloride - Nasal Decongestant

Cold, Flu & Hay Fever Multi-Symptom Relief
■ Minor Aches & Pain, Sore Throat
■ Headache, Fever
■ Nasal Congestion, Sinus Pressure/Drainage

36 Tablets

In Individually Sealed Strip

Aspirin Free